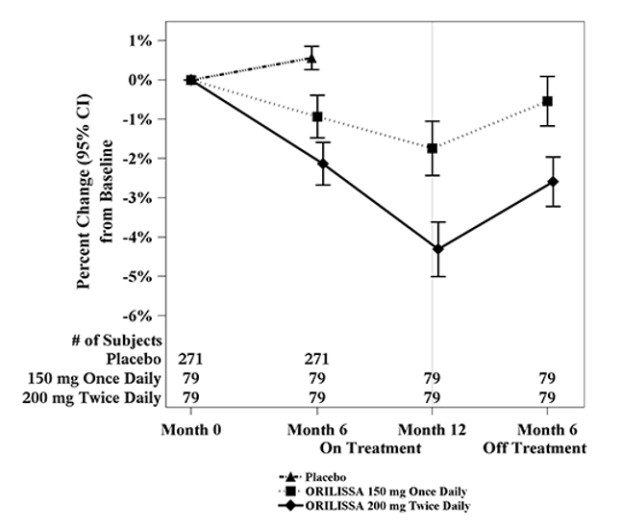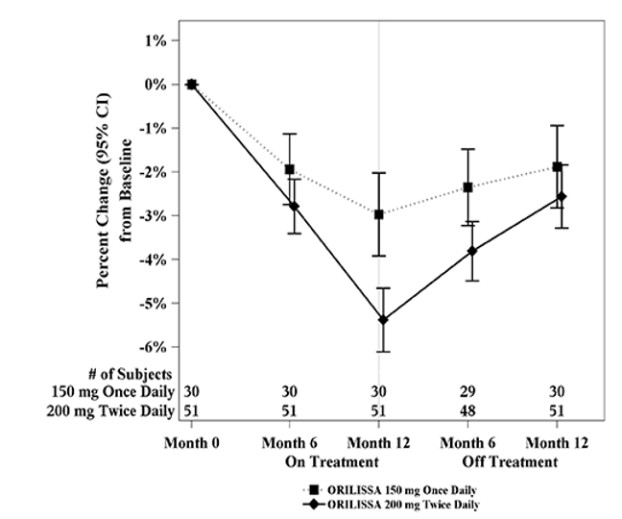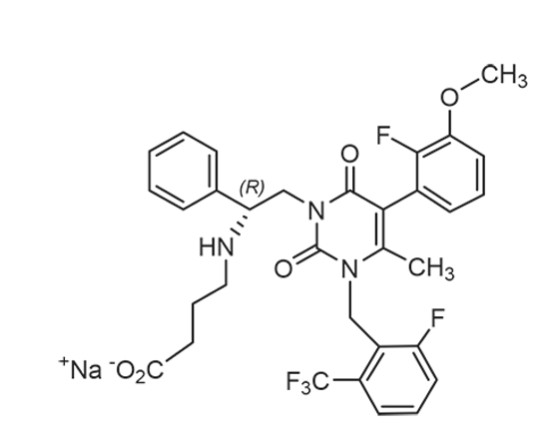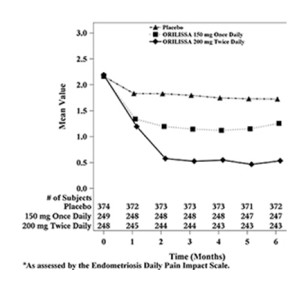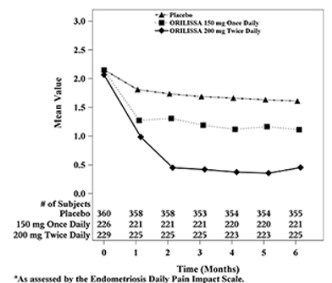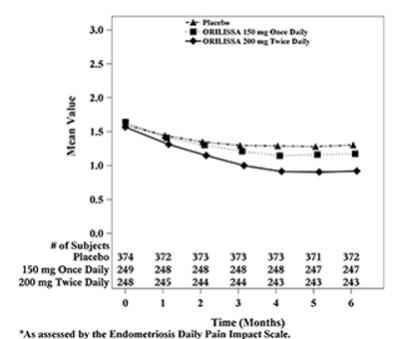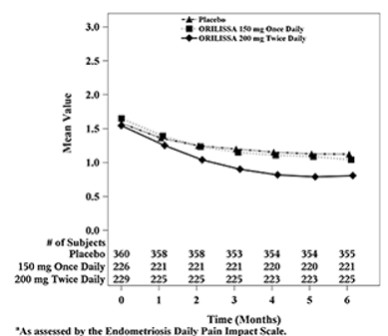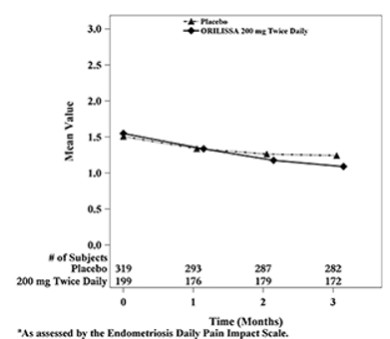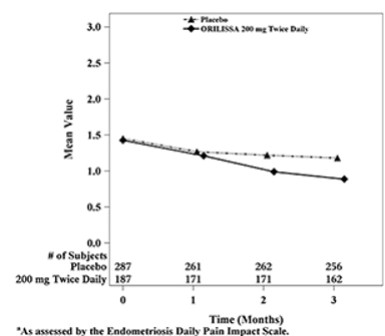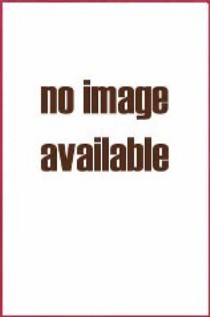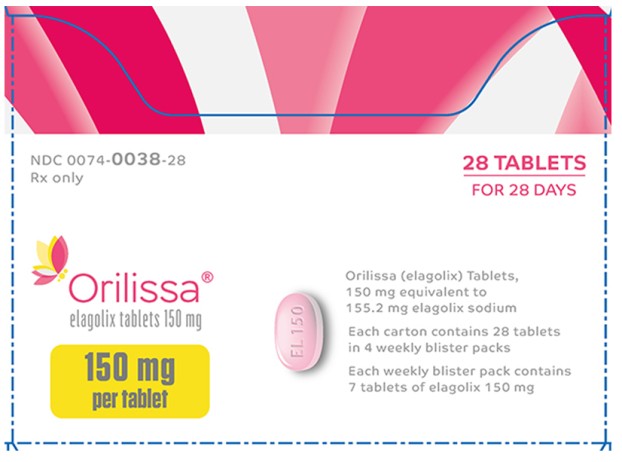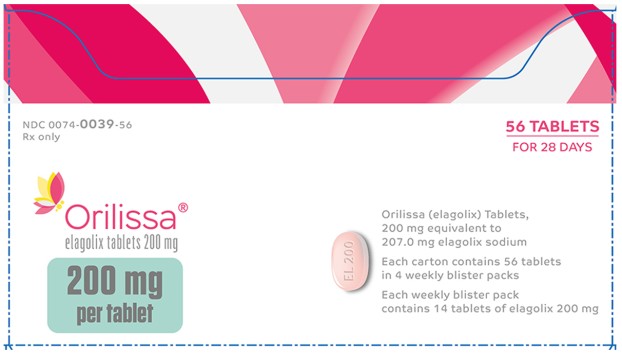 DRUG LABEL: Orilissa
NDC: 0074-0038 | Form: TABLET, FILM COATED
Manufacturer: AbbVie Inc.
Category: prescription | Type: HUMAN PRESCRIPTION DRUG LABEL
Date: 20251219

ACTIVE INGREDIENTS: ELAGOLIX SODIUM 150 mg/1 1
INACTIVE INGREDIENTS: MANNITOL; SODIUM CARBONATE MONOHYDRATE; STARCH, CORN; POVIDONE, UNSPECIFIED; MAGNESIUM STEARATE; POLYVINYL ALCOHOL, UNSPECIFIED; TITANIUM DIOXIDE; POLYETHYLENE GLYCOL, UNSPECIFIED; TALC; CARMINIC ACID

HIGHLIGHTS OF PRESCRIBING INFORMATION

These highlights do not include all the information needed to use ORILISSA safely and effectively. See full prescribing information for ORILISSA.
ORILISSA® (elagolix) tablets, for oral use
Initial U.S. Approval: 2018

1 INDICATIONS AND USAGE

ORILISSA is a gonadotropin-releasing hormone (GnRH) receptor antagonist indicated for the management of moderate to severe pain associated with endometriosis. (1)

Limitations of Use:

- Limit the duration of use based on the dose and coexisting condition (see Table 1). (1)

2 DOSAGE AND ADMINISTRATION

Normal liver function or mild hepatic impairment: 150 mg once daily for up to 24 months or 200 mg twice daily for up to 6 months. (2.1)

Moderate hepatic impairment: 150 mg once daily for up to 6 months. (2.1)

3 DOSAGE FORMS AND STRENGTHS

Oral tablets: 150 mg and 200 mg (3)

4 CONTRAINDICATIONS

- Pregnancy (4)
- Known osteoporosis (4)
- Severe hepatic impairment (4)
- Organic anion transporting polypeptide (OATP) 1B1 inhibitors that significantly increase elagolix plasma concentrations (4)
- Hypersensitivity reactions (4, 6.2)

5 WARNINGS AND PRECAUTIONS

- Bone Loss: Dose- and duration-dependent decreases in bone mineral density (BMD) that may not be completely reversible. Assess BMD in women with additional risk factors for bone loss (5.1)
- Reduced Ability to Recognize Pregnancy: ORILISSA may alter menstrual bleeding, which may reduce the ability to recognize pregnancy. Perform testing if pregnancy is suspected. Discontinue if pregnancy is confirmed (5.2)
- Suicidal Ideation and Mood Disorders: Advise patients to seek medical attention for suicidal ideation, suicidal behavior, new onset or worsening depression, anxiety, or other mood changes (5.3)
- Hepatic Transaminase Elevations: Dose-dependent elevations in serum alanine aminotransferase (ALT). Counsel patients on signs and symptoms of liver injury (5.4)
- Interactions with Hormonal Contraceptives: Use non-hormonal contraception during treatment and for 28 days after discontinuing ORILISSA. Coadministration of ORILISSA 200 mg twice daily with an estrogen-containing contraceptive is not recommended because of the potential for increased estrogen-associated risks. Coadministration of ORILISSA with an estrogen-containing contraceptive may reduce the efficacy of ORILISSA. Coadministration with progestin-containing oral contraceptives may reduce the efficacy of the contraceptive. (5.5)

6 ADVERSE REACTIONS

Most common adverse reactions (>5%) in clinical trials included hot flushes and night sweats, headache, nausea, insomnia, amenorrhea, anxiety, arthralgia, depression-related adverse reactions and mood changes (6.1).

To report SUSPECTED ADVERSE REACTIONS, contact AbbVie Inc. at 1-800-633-9110 or FDA at 1-800-FDA-1088 or www.fda.gov/medwatch

7 DRUG INTERACTIONS

See full prescribing information for a list of clinically important drug interactions (7).

FULL PRESCRIBING INFORMATION

1 INDICATIONS AND USAGE

ORILISSA is indicated for the management of moderate to severe pain associated with endometriosis.

Limitations of Use:

Limit the duration of use based on the dose and coexisting condition (see Table 1) [see Dosage and Administration (2.1) and Warnings and Precautions (5.1)].

2 DOSAGE AND ADMINISTRATION

2.1 Important Dosing Information

- Exclude pregnancy before starting ORILISSA or start ORILISSA within 7 days from the onset of menses.
- Take ORILISSA at approximately the same time each day, with or without food.
- Use the lowest effective dose, taking into account the severity of symptoms and treatment objectives [see Warnings and Precautions (5.1, 5.3, 5.4) and Clinical Studies (14)].
- Limit the duration of use because of bone loss (Table 1) [see Warnings and Precautions (5.1)].

Table 1. Recommended Dosage and Duration of Use
Dosing Regimen | Maximum Treatment Duration | Coexisting Condition
Initiate treatment with ORILISSA 150 mg once daily | 24 months | None
Consider initiating treatment with ORILISSA 200 mg twice daily | 6 months | Dyspareunia
Initiate treatment with ORILISSA 150 mg once daily. Use of 200 mg twice daily is not recommended. | 6 months | Moderate hepatic impairment (Child-Pugh Class B)

2.2 Hepatic Impairment

No dosage adjustment of ORILISSA is required in women with mild hepatic impairment (Child-Pugh A).

Compared to women with normal liver function, those with moderate hepatic impairment had approximately 3-fold higher elagolix exposures and those with severe hepatic impairment had approximately 7-fold higher elagolix exposures. Because of these increased exposures and risk for bone loss:

- ORILISSA 150 mg once daily is recommended for women with moderate hepatic impairment (Child-Pugh B) with the duration of treatment limited to 6 months. Use of ORILISSA 200 mg twice daily is not recommended for women with moderate hepatic impairment [see Use in Specific Populations (8.7) and Clinical Pharmacology (12.3)].
- ORILISSA is contraindicated in women with severe hepatic impairment (Child-Pugh C) [see Contraindications (4), Use in Specific Populations (8.7) and Clinical Pharmacology (12.3)].

2.3 Missed Dose

Instruct the patient to take a missed dose of ORILISSA on the same day as soon as she remembers and then resume the regular dosing schedule.

- 150 mg once daily: take no more than 1 tablet each day.
- 200 mg twice daily: take no more than 2 tablets each day.

3 DOSAGE FORMS AND STRENGTHS

The 150 mg tablets are light pink, oblong, film-coated tablets with “EL 150” debossed on one side. Each tablet contains 155.2 mg of elagolix sodium equivalent to 150 mg of elagolix.

The 200 mg tablets are light orange, oblong, film-coated tablets with “EL 200” debossed on one side. Each tablet contains 207.0 mg of elagolix sodium equivalent to 200 mg of elagolix.

4 CONTRAINDICATIONS

ORILISSA is contraindicated in women:

- Who are pregnant [see Use in Specific Populations (8.1)]. Exposure to ORILISSA early in pregnancy may increase the risk of early pregnancy loss.
- With known osteoporosis because of the risk of further bone loss [see Warnings and Precautions (5.1)]
- With severe hepatic impairment [see Use in Specific Populations (8.7), Clinical Pharmacology (12.3)]
- Taking inhibitors of organic anion transporting polypeptide (OATP)1B1 (a hepatic uptake transporter) that are known or expected to significantly increase elagolix plasma concentrations [see Drug Interactions (7.2)]
- With known hypersensitivity reaction to ORILISSA or any of its inactive components. Reactions have included anaphylaxis and angioedema [see Adverse Reactions (6.2)].

5 WARNINGS AND PRECAUTIONS

5.1 Bone Loss

ORILISSA causes a dose-dependent decrease in bone mineral density (BMD). BMD loss is greater with increasing duration of use and may not be completely reversible after stopping treatment [see Adverse Reactions (6.1)]. The impact of these BMD decreases on long-term bone health and future fracture risk are unknown.

ORILISSA is contraindicated in women with known osteoporosis [see Contraindications (4)]. Consider assessment of BMD in patients with a history of a low-trauma fracture or other risk factors for osteoporosis or bone loss. Limit the duration of use to reduce the extent of bone loss [see Dosage and Administration (2.2)]. Although the effect of supplementation with calcium and vitamin D was not studied, such supplementation may be beneficial for all patients.

5.2 Change in Menstrual Bleeding Pattern and Reduced Ability to Recognize Pregnancy

Women who take ORILISSA may experience a reduction in the amount, intensity or duration of menstrual bleeding, which may reduce the ability to recognize the occurrence of a pregnancy in a timely manner [see Adverse Reactions (6.1)]. Perform pregnancy testing if pregnancy is suspected, and discontinue ORILISSA if pregnancy is confirmed.

5.3 Suicidal Ideation, Suicidal Behavior, and Exacerbation of Mood Disorders

Suicidal ideation and behavior, including one completed suicide, occurred in subjects treated with ORILISSA in the endometriosis clinical trials. ORILISSA subjects had a higher incidence of depression and mood changes compared to placebo, and ORILISSA subjects with a history of suicidality or depression had a higher incidence of depression compared to subjects without such a history [see Adverse Reactions (6.1)]. Promptly evaluate patients with depressive symptoms to determine whether the risks of continued therapy outweigh the benefits [see Adverse Reactions (6.1)]. Patients with new or worsening depression, anxiety or other mood changes should be referred to a mental health professional, as appropriate. Advise patients to seek immediate medical attention for suicidal ideation and behavior. Reevaluate the benefits and risks of continuing ORILISSA if such events occur.

5.4 Hepatic Transaminase Elevations

In clinical trials, dose-dependent elevations of serum alanine aminotransferase (ALT) at least 3-times the upper limit of the reference range occurred with ORILISSA. Use the lowest effective dose of ORILISSA and instruct patients to promptly seek medical attention in case of symptoms or signs that may reflect liver injury, such as jaundice. Promptly evaluate patients with elevations in liver tests to determine whether the benefits of continued therapy outweigh the risks [see Adverse Reactions (6.1)].

5.5 Interactions with Hormonal Contraceptives

Advise women to use effective non-hormonal contraceptives during treatment with ORILISSA and for 28 days after discontinuing ORILISSA [see Use in Specific Populations (8.1, 8.3), Drug Interactions (7.1), Clinical Pharmacology (12.3)].

Increase in Estrogen Exposure and Potential Associated Increased Risks When ORILISSA 200 mg Twice Daily is Taken With Combined Hormonal Contraceptives

Co-administration of a combined oral contraceptive (COC) (containing 20 mcg ethinyl estradiol/0.1 mg levonorgestrel) following administration of ORILISSA 200 mg twice daily for 14 days increases the plasma ethinyl estradiol concentration by 2.2-fold compared to this COC alone. ORILISSA 200 mg twice daily co-administered with a COC containing ethinyl estradiol may lead to increased risk of ethinyl estradiol-related adverse events including thromboembolic disorders and vascular events and is not recommended [see Drug Interactions (7.1), Clinical Pharmacology (12.3)].

Potential for Reduced Efficacy of Progestin-Containing Hormonal Contraceptives

Co-administration of ORILISSA 200 mg twice daily and a COC containing 0.1 mg levonorgestrel decreases the plasma concentrations of levonorgestrel by 27%, potentially affecting contraceptive efficacy. Co-administration of ORILISSA with COCs containing norethindrone acetate did not show reduction in plasma concentrations of norethindrone [see Drug Interactions (7.1), Clinical Pharmacology (12.3)].

Co-administration of ORILISSA with progestin-containing intrauterine contraceptive systems has not been studied.

Reduced efficacy of ORILISSA

Based on the mechanism of action of ORILISSA, estrogen-containing contraceptives are expected to reduce the efficacy of ORILISSA. The effect of progestin-only contraceptives on the efficacy of ORILISSA is unknown.

6 ADVERSE REACTIONS

The following serious adverse reactions are discussed elsewhere in labeling:

- Bone loss [see Warnings and Precautions (5.1)]
- Change in menstrual bleeding pattern and reduced ability to recognize pregnancy [see Warnings and Precautions (5.2)]
- Suicidal ideation, suicidal behavior, and exacerbation of mood disorders [see Warnings and Precautions (5.3)]
- Hepatic transaminase elevations [see Warnings and Precautions (5.4)]

6.1 Clinical Trials Experience

Because clinical trials are conducted under widely varying conditions, adverse reaction rates observed in the clinical trials of a drug cannot be directly compared to rates in the clinical trials of another drug and may not reflect the rates observed in clinical practice.

The safety of ORILISSA was evaluated in two six-month, randomized, double-blind, placebo-controlled clinical trials [EM-1 (NCT01620528) and EM-2 (NCT01931670)] in which a total of 952 adult women with moderate to severe pain associated with endometriosis were treated with ORILISSA (475 with 150 mg once daily and 477 with 200 mg twice daily) and 734 were treated with placebo. The population age range was 18-49 years old. Women who completed six months of treatment and met eligibility criteria continued treatment in two uncontrolled, blinded six-month extension trials [EM-3 (NCT01760954) and EM-4 (NCT02143713)], for a total treatment duration of up to 12 months.

Serious Adverse Events

Overall, the most common serious adverse events reported for subjects treated with ORILISSA in the two placebo-controlled clinical trials (Studies EM-1 and EM-2) included appendicitis (0.3%), abdominal pain (0.2%), and back pain (0.2%). In these trials, 0.2% of subjects treated with ORILISSA 150 mg once daily and 0.2% of subjects treated with ORILISSA 200 mg twice daily discontinued therapy due to serious adverse reactions compared to 0.5% of those given placebo.

Adverse Reactions Leading to Study Discontinuation

In the two placebo-controlled clinical trials (Studies EM-1 and EM-2), 5.5% of subjects treated with ORILISSA 150 mg once daily and 9.6% of subjects treated with ORILISSA 200 mg twice daily discontinued therapy due to adverse reactions compared to 6.0% of those given placebo. Discontinuations were most commonly due to hot flushes or night sweats (1.1% with 150 mg once daily and 2.5% with 200 mg twice daily) and nausea (0.8% with 150 mg once daily and 1.5% with 200 mg twice daily) and were dose-related. The majority of discontinuations due to hot flushes or night sweats (10 of 17, 59%) and nausea (7 of 11, 64%) occurred within the first 2 months of therapy.

In the two extension trials (Studies EM-3 and EM-4), discontinuations were most commonly due to decreased BMD and were dose-related. In these trials, 0.3% of subjects treated with ORILISSA 150 mg once daily and 3.6% of subjects treated with ORILISSA 200 mg twice daily discontinued therapy due to decreased BMD.

Common Adverse Reactions:

Adverse reactions reported in ≥ 5% of women in the two placebo-controlled trials in either ORILISSA dose group and at a greater frequency than placebo are noted in the following table.

Table 2. Percentage of Subjects in Studies EM-1 and EM-2 with Treatment-Emergent Adverse Reactions Occurring in at Least 5% of Subjects (either ORILISSA Dose Group) and at a Greater Incidence than with Placebo
 | ORILISSA 150 mg Once Daily N=475 | ORILISSA 200 mg Twice Daily N=477 | Placebo N=734
 | % | % | %
Hot Flush | 24 | 46 | 9
Headache | 17 | 20 | 12
Nausea | 11 | 16 | 13
Insomnia | 6 | 9 | 3
Mood altered, mood swings | 6 | 5 | 3
Amenorrhea | 4 | 7 | <1
Depressed mood, depression, depressive symptoms and/or tearfulness | 3 | 6 | 2
Anxiety | 3 | 5 | 3
Arthralgia | 3 | 5 | 3

The most commonly reported adverse reactions in the extension trials (EM-3 and EM-4) were similar to those in the placebo-controlled trials.

Less Common Adverse Reactions:

In Study EM-1 and Study EM-2, adverse reactions reported in ≥ 3% and < 5% in either ORILISSA dose group and greater than placebo included: decreased libido, diarrhea, abdominal pain, weight gain, dizziness, constipation and irritability.

Bone Loss

The effect of ORILISSA on BMD was assessed by dual-energy X-ray absorptiometry (DXA).

In Studies EM-1 and EM-2, there was a dose-dependent decrease in BMD in ORILISSA-treated subjects compared to an increase in placebo-treated subjects.

In Study EM-1, compared to placebo, the mean change from baseline in lumbar spine BMD at 6 months was -0.9% (95% CI: -1.3, -0.4) with ORILISSA 150 mg once daily and -3.1% (95% CI: -3.6, -2.6) with ORILISSA 200 mg twice daily (Table 3). The percentage of subjects with greater than 8% BMD decrease in lumbar spine, total hip or femoral neck at any time point during the placebo-controlled treatment period was 2% with ORILISSA 150 mg once daily, 7% with ORILISSA 200 mg twice daily and < 1% with placebo. In the blinded extension Study EM-3, continued bone loss was observed with 12 months of continuous treatment with ORILISSA. The percentage of subjects with greater than 8% BMD decrease in lumbar spine, total hip or femoral neck at any time point during the extension treatment period was 8% with continuous ORILISSA 150 mg once daily and 21% with continuous ORILISSA 200 mg twice daily.

In Study EM-2, compared to placebo, the mean change from baseline in lumbar spine BMD at 6 months was -1.3% (95% CI: -1.8, -0.8) with ORILISSA 150 mg once daily and -3.0% (95% CI: -3.5, -2.6) with ORILISSA 200 mg twice daily (Table 3). The percentage of subjects with greater than 8% BMD decrease in lumbar spine, total hip or femoral neck at any time point during the placebo-controlled treatment period was < 1% with ORILISSA 150 mg once daily, 6% with ORILISSA 200 mg twice daily and 0% with placebo. In the blinded extension Study EM-4, continued bone loss was observed with 12 months of continuous treatment with ORILISSA. The percentage of subjects with greater than 8% BMD decrease in lumbar spine, total hip or femoral neck at any time point during the extension treatment period was 2% with continuous ORILISSA 150 mg once daily and 21% with continuous ORILISSA 200 mg twice daily.

Table 3. Percent Change from Baseline in Lumbar Spine BMD at Month 6
 | ORILISSA 150 mg Once Daily | ORILISSA 200 mg Twice Daily | Placebo
EM-1
N | 183 | 180 | 277
Percent Change from Baseline, % | -0.3 | -2.6 | 0.5
Treatment Difference, % (95% CI) | -0.9 (-1.3, -0.4) | -3.1 (-3.6, -2.6)
EM-2
N | 174 | 183 | 271
Percent Change from Baseline, % | -0.7 | -2.5 | 0.6
Treatment Difference, % (95% CI) | -1.3 (-1.8, -0.8) | -3.0 (-3.5, -2.6)

To assess for recovery, the change in lumbar spine BMD over time was analyzed for subjects who received continuous treatment with ORILISSA 150 mg once daily or ORILISSA 200 mg twice daily for up to 12 months and who were then followed after cessation of therapy for an additional 6 months. Partial recovery of BMD was seen in these subjects (Figure 1).

In Study EM-3, if a subject had BMD loss of more than 1.5% at the lumbar spine or more than 2.5% at the total hip at the end of treatment, follow-up DXA was required after 6 months off-treatment. In Study EM-4, all subjects were required to have a follow-up DXA 6 months off treatment regardless of change in BMD and if a subject had BMD loss of more than 1.5% at the lumbar spine or more than 2.5% at the total hip after 6 months off treatment, follow-up DXA was required after 12 months off-treatment. Figure 2 shows the change in lumbar spine BMD for the subjects in Study EM-2/EM-4 who completed 12 months of treatment with ORILISSA and who had a follow-up DXA 12-months off treatment.

Figure 1. Percent Change from Baseline in Lumbar Spine BMD in Subjects Who Received 12 Months of ORILISSA and Had Follow-up BMD 6 Months off Therapy in Studies EM-2/EM-4

Figure 2. Percent Change from Baseline in Lumbar Spine BMD in Subjects Who Received 12 Months of ORILISSA and Had Follow-up BMD 12 Months off Therapy in Studies EM-2/EM-4

Suicidal Ideation, Suicidal Behavior and Exacerbation of Mood Disorders

In the placebo-controlled trials (Studies EM-1 and EM-2), ORILISSA was associated with adverse mood changes (see Table 2 and Table 4), particularly in those with a history of depression.

Table 4. Suicidal Ideation and Suicidal Behavior in Studies EM-1 and EM-2
Adverse Reactions | ORILISSA
 | 150 mg Once Daily (N=475) n (%) | 200 mg Twice Daily (N=477) n (%) | Placebo (N=734) n (%)
Completed suicide | 1 (0.2) | 0 | 0
Suicidal ideation | 1 (0.2) | 1 (0.2) | 0

A 44-year-old woman received 31 days of ORILISSA 150 mg once daily then completed suicide 2 days after ORILISSA discontinuation. She had no relevant past medical history; life stressors were noted.

Among the 2090 subjects exposed to ORILISSA in the endometriosis Phase 2 and Phase 3 studies, there were four reports of suicidal ideation. In addition to the two subjects in Table 4, there were two additional reports of suicidal ideation: one subject in EM-3 (150 mg once daily) and one in a Phase 2 study (75 mg once daily, an unapproved dose). Three of these subjects had a history of depression. Two subjects discontinued ORILISSA and two completed the clinical trial treatment periods.

Hepatic Transaminase Elevations

In the placebo-controlled clinical trials (Studies EM-1 and EM-2), dose-dependent asymptomatic elevations of serum ALT to at least 3-times the upper limit of the reference range occurred during treatment with ORILISSA (150 mg once daily – 1/450, 0.2%; 200 mg twice daily – 5/443, 1.1%; placebo – 1/696, 0.1%). Similar increases were seen in the extension trials (Studies EM-3 and EM-4).

Changes in Lipid Parameters

Dose-dependent increases in total cholesterol, low-density lipoprotein cholesterol (LDL-C), high density lipoprotein cholesterol (HDL-C), and serum triglycerides were noted during ORILISSA treatment in EM-1 and EM-2. In EM-1 and EM-2, 12% and 1% of subjects with mildly elevated LDL-C (130-159 mg/dL) at baseline had an increase in LDL-C concentrations to 190 mg/dL or higher during treatment with ORILISSA and placebo, respectively. In EM-1 and EM-2, 4% and 1% of subjects with mildly elevated serum triglycerides (150-300 mg/dL) at baseline had an increase in serum triglycerides to at least 500 mg/dL during treatment with ORILISSA and placebo, respectively. The highest measured serum triglyceride concentration during treatment with ORILISSA was 982 mg/dL.

Table 5. Mean Change and Maximum Increase from Baseline in Serum Lipids in Studies EM-1 and EM-2
 | ORILISSA 150 mg Once Daily N=475 | ORILISSA 200 mg Twice Daily N=477 | Placebo N=734
LDL-C (mg/dL)
Mean change at Month 6 | 5 | 13 | -3
Maximum increase during Treatment Period | 137 | 107 | 122
HDL-C (mg/dL)
Mean change at Month 6 | 2 | 4 | 1
Maximum increase during Treatment Period | 43 | 52 | 45
Triglycerides (mg/dL)
Mean change at Month 6 | <1 | 11 | -3
Maximum increase during Treatment Period | 624 | 484 | 440

Lipid increases occurred within 1 to 2 months after the start of ORILISSA and remained stable thereafter over 12 months.

Hypersensitivity Reactions

In Studies EM-1 and EM-2, non-serious hypersensitivity reactions including rash occurred in 5.8% of ORILISSA treated-subjects and 6.1% of placebo-treated subjects. These events led to study drug discontinuation in 0.4% of ORILISSA-treated subjects and 0.5% of placebo-treated subjects.

Effects on Menstrual Bleeding Patterns

The effects of ORILISSA on menstrual bleeding were evaluated for up to 12 months using an electronic daily diary where subjects classified their flow of menstrual bleeding (if present in the last 24 hours) as spotting, light, medium, or heavy. ORILISSA led to a dose-dependent reduction in mean number of bleeding and spotting days and bleeding intensity in those subjects who reported menstrual bleeding.

Table 6. Mean Bleeding/Spotting Days and Mean Intensity Scores at Month 3
 | ORILISSA 150mg Once Daily |  | ORILISSA 200mg Twice Daily |  | Placebo
 | Baseline | Month 3 | Baseline | Month 3 | Baseline | Month 3
Mean bleeding/ spotting days in prior 28 days | 5.3 | 2.8 | 5.7 | 0.8 | 5.4 | 4.6
Mean Intensity scorea | 2.6 | 2.2 | 2.5 | 2.0 | 2.6 | 2.4
aIntensity for subjects who reported at least 1 day of bleeding or spotting during 28 day interval. Scale ranges from 1 to 4, 1 = spotting, 2 = light, 3 = medium, 4 = heavy

ORILISSA also demonstrated a dose-dependent increase in the percentage of women with amenorrhea (defined as no bleeding or spotting in a 56-day interval) over the treatment period. The incidence of amenorrhea during the first six months of treatment ranged from 6-17% for ORILISSA 150 mg once daily, 13-52% for ORILISSA 200 mg twice daily and less than 1% for placebo. During the second 6 months of treatment, the incidence of amenorrhea ranged from 11-15% for ORILISSA 150 mg once daily and 46-57% for ORILISSA 200 mg twice daily.

After 6 months of therapy with ORILISSA 150 mg once daily, resumption of menses after stopping treatment was reported by 59%, 87% and 95% of women within 1, 2, and 6 months, respectively. After 6 months of therapy with ORILISSA 200 mg twice daily, resumption of menses after stopping treatment was reported by 60%, 88%, and 97% of women within 1, 2, and 6 months, respectively.

After 12 months of therapy with ORILISSA 150 mg once daily resumption of menses after stopping treatment was reported by 77%, 95% and 98% of women within 1, 2, and 6 months respectively. After 12 months of therapy with ORILISSA 200 mg twice daily resumption of menses after stopping treatment was reported by 55%, 91% and 96% of women within 1, 2, and 6 months respectively.

6.2 Postmarketing Experience

The following adverse reactions have been identified during post-approval use of ORILISSA. Because these reactions are reported voluntarily from a population of uncertain size, it is not always possible to reliably estimate their frequency or establish a causal relationship to drug exposure.

Immune system disorders: hypersensitivity reactions (including anaphylaxis, angioedema, and urticaria).

7 DRUG INTERACTIONS

7.1 Potential for ORILISSA to Affect Other Drugs

Elagolix is:

- A weak to moderate inducer of cytochrome P450 (CYP) 3A. Co-administration with ORILISSA may decrease plasma concentrations of drugs that are substrates of CYP3A (see Table 7).
- A weak inhibitor of CYP 2C19. Co-administration with ORILISSA may increase plasma concentrations of drugs that are substrates of CYP2C19 (see Table 7).
- An inhibitor of efflux transporter P-glycoprotein (P-gp). Co-administration with ORILISSA may increase plasma concentrations of drugs that are substrates of P-gp (see Table 7).

The effects of co-administration of ORILISSA on concentrations of concomitant drugs and the clinical recommendations for these drug interactions are summarized in Table 7.

Table 7. Drug Interactions: Effects of ORILISSA on Other Drugs
Concomitant Drug Class: Drug Name | Effect on Plasma Exposure of Concomitant Drug | Clinical Recommendations
Cardiac glycosides: digoxin | ↑ digoxin | Increase monitoring of digoxin concentrations and potential signs and symptoms of clinical toxicity when initiating ORILISSA in patients who are taking digoxin. If ORILISSA is discontinued, increase monitoring of digoxin concentrations.
Benzodiazepines: oral midazolam | ↓ midazolam | Consider increasing the dose of midazolam by no more than 2-fold and individualize midazolam therapy based on the patient’s response.
Statins: rosuvastatin | ↓ rosuvastatin | Monitor lipid levels and adjust the dose of rosuvastatin, if necessary.
Proton pump inhibitors: omeprazole | ↑ omeprazole | No dose adjustment needed for omeprazole 40 mg once daily when co-administered with ORILISSA. When ORILISSA is used concomitantly with higher doses of omeprazole, consider dosage reduction of omeprazole.
Combined hormonal contraceptives: oral ethinyl estradiol/levonorgestrel | ↑ethinyl estradiol ↓levonorgestrel | Advise women to use effective non-hormonal contraception during treatment with ORILISSA and for 28 days after discontinuing ORILISSA.
See Tables 10 and 11 [see Clinical Pharmacology (12.3)].
The direction of the arrow indicates the direction of the change in the area under the curve (AUC) (↑= increase, ↓ = decrease).

7.2 Potential for Other Drugs to Affect ORILISSA

Elagolix is a substrate of CYP3A, P-gp, and OATP1B1.

Concomitant use of ORILISSA 200 mg twice daily and strong CYP3A inhibitors for more than 1 month is not recommended. Limit concomitant use of ORILISSA 150 mg once daily and strong CYP3A inhibitors to 6 months.

Co-administration of ORILISSA with strong CYP3A inducers may decrease elagolix plasma concentrations and may result in a decrease of the therapeutic effects of ORILISSA.

Concomitant use of ORILISSA 200 mg twice daily and rifampin is not recommended. Limit concomitant use of ORILISSA 150 mg once daily and rifampin to 6 months.

The effect of concomitant use of P-gp inhibitors or inducers on the pharmacokinetics of ORILISSA is unknown. OATP1B1 inhibitors that are known or expected to significantly increase elagolix plasma concentrations are contraindicated due to increased risk of elagolix-associated adverse reactions [see Contraindications (4)].

8 USE IN SPECIFIC POPULATIONS

8.1 Pregnancy

Risk Summary

Use of ORILISSA is contraindicated in pregnant women. Exposure to ORILISSA early in pregnancy may increase the risk of early pregnancy loss. Discontinue ORILISSA if pregnancy occurs during treatment.

The limited human data with the use of ORILISSA in pregnant women are insufficient to determine whether there is a risk for major birth defects or miscarriage. Although two cases of congenital malformations were reported in clinical trials with ORILISSA, no pattern was identified and miscarriages were reported at a similar incidence across treatment groups (see Data).

When pregnant rats and rabbits were orally dosed with elagolix during the period of organogenesis, postimplantation loss was observed in pregnant rats at doses 20 times the maximum recommended human dose (MRHD). Spontaneous abortion and total litter loss was observed in rabbits at doses 7 and 12 times the MRHD. There were no structural abnormalities in the fetuses at exposures up to 40 and 12 times the MRHD for the rat and rabbit, respectively (see Data).

Data

Human Data

There were 49 pregnancies reported in clinical trials of more than 3,500 women (of whom more than 2,000 had endometriosis) treated with ORILISSA for up to 12 months. These pregnancies occurred while the women were receiving ORILISSA or within 30 days after stopping ORILISSA. Among these 49 pregnancies, two major congenital malformations were reported. In one case of infant cleft palate, the mother was treated with ORILISSA 150 mg daily and the estimated fetal exposure to ORILISSA occurred during the first 30 days of pregnancy. In one case of infant tracheoesophageal fistula, the mother was treated with ORILISSA 150 mg daily and the estimated fetal exposure to ORILISSA occurred during the first 15 days of pregnancy.

Among these 49 pregnancies, there were five cases of spontaneous abortion (miscarriage) compared to five cases among the 20 pregnancies that occurred in more than 1100 women treated with placebo. Although the duration of fetal exposure was limited in ORILISSA clinical trials, there were no apparent decreases in birth weights associated with ORILISSA in comparison to placebo.

Animal Data

Embryofetal development studies were conducted in the rat and rabbit. Elagolix was administered by oral gavage to pregnant rats (25 animals/dose) at doses of 0, 300, 600 and 1200 mg/kg/day and to rabbits (20 animals/dose) at doses of 0, 100, 150, and 200 mg/kg/day, during the period of organogenesis (gestation day 6-17 in the rat and gestation day 7-20 in the rabbit).

In rats, maternal toxicity was present at all doses and included six deaths and decreases in body weight gain and food consumption. Increased postimplantation losses were present in the mid dose group, which was 20 times the MRHD based on AUC. In rabbits, three spontaneous abortions and a single total litter loss were observed at the highest, maternally toxic dose, which was 12 times the MRHD based on AUC. A single total litter loss occurred at a lower non-maternally toxic dose of 150 mg/kg/day, which was 7 times the MRHD.

No fetal malformations were present at any dose level tested in either species even in the presence of maternal toxicity. At the highest doses tested, the exposure margins were 40 and 12 times the MRHD for the rat and rabbit, respectively. However, because elagolix binds poorly to the rat gonadotropin-releasing hormone (GnRH) receptor (~1000 fold less than to the human GnRH receptor), the rat study is unlikely to identify pharmacologically mediated effects of elagolix on embryofetal development. The rat study is still expected to provide information on potential non-target-related effects of elagolix.

In a pre- and postnatal development study in rats, elagolix was given in the diet to achieve doses of 0, 100 and 300 mg/kg/day (25 per dose group) from gestation day 6 to lactation day 20. There was no evidence of maternal toxicity. At the highest dose, two dams had total litter loss, and one failed to deliver. Pup survival was decreased from birth to postnatal day 4. Pups had lower birth weights and lower body weight gains were observed throughout the pre-weaning period at 300 mg/kg/day. Smaller body size and effect on startle response were associated with lower pup weights at 300 mg/kg/day. Post-weaning growth, development and behavioral endpoints were unaffected.

Maternal plasma concentrations in rats on lactation day 21 at 100 and 300 mg/kg/day (47 and 125 ng/mL) were 0.06-fold and 0.16-fold the maximal elagolix concentration (Cmax) in humans at the MRHD. Because the exposures achieved in rats were much lower than the human MRHD, this study is not predictive of potentially higher lactational exposure in humans.

8.2 Lactation

Risk Summary

There is no information on the presence of elagolix or its metabolites in human milk, the effects on the breastfed child, or the effects on milk production. There are no adequate animal data on the excretion of ORILISSA in milk. The developmental and health benefits of breastfeeding should be considered along with the mother’s clinical need for ORILISSA and any potential adverse effects on the breastfed child from ORILISSA.

Data

There are no adequate animal data on excretion of elagolix in milk.

8.3 Females and Males of Reproductive Potential

Based on the mechanism of action, there is a risk of early pregnancy loss if ORILISSA is administered to a pregnant woman [see Use in Specific Populations (8.1), Clinical Pharmacology (12.1)].

Pregnancy Testing

ORILISSA may delay the ability to recognize the occurrence of a pregnancy because it may reduce the intensity, duration, and amount of menstrual bleeding. Exclude pregnancy before initiating treatment with ORILISSA. Perform pregnancy testing if pregnancy is suspected during treatment with ORILISSA and discontinue treatment if pregnancy is confirmed [see Contraindications (4) and Warnings and Precautions (5.2)].

Contraception

Advise women to use effective non-hormonal contraception during treatment with ORILISSA and for 28 days after discontinuing ORILISSA [see Warnings and Precautions (5.5)].

8.4 Pediatric Use

Safety and effectiveness of ORILISSA in pediatric patients have not been established.

8.6 Renal Impairment

No dose adjustment of ORILISSA is required in women with any degree of renal impairment or end-stage renal disease (including women on dialysis) [see Clinical Pharmacology (12.3)].

8.7 Hepatic Impairment

No dosage adjustment of ORILISSA is required for women with mild hepatic impairment (Child-Pugh A). Only the 150 mg once daily regimen is recommended for women with moderate hepatic impairment (Child-Pugh B) and the duration of treatment should be limited to 6 months.

ORILISSA is contraindicated in women with severe hepatic impairment (Child-Pugh C) [see Contraindications (4), and Clinical Pharmacology (12.3)].

10 OVERDOSAGE

In case of overdose, monitor the patient for any signs or symptoms of adverse reactions and initiate appropriate symptomatic treatment, as needed.

11 DESCRIPTION

ORILISSA (elagolix) tablets for oral administration contain elagolix sodium, the sodium salt of the active moiety elagolix. Elagolix sodium is a nonpeptide small molecule, GnRH receptor antagonist. Elagolix sodium is chemically described as sodium 4-({(1R)-2-[5-(2-fluoro-3-methoxyphenyl)-3-{[2-fluoro-6-(trifluoromethyl)phenyl]methyl}-4-methyl-2,6-dioxo-3,6-dihydropyrimidin-1(2H)-yl]-1-phenylethyl}amino)butanoate. Elagolix sodium has a molecular formula of C32H29F5N3O5Na and a molecular weight of 653.58. Elagolix free acid has a molecular weight of 631.60.

Elagolix sodium has the following structural formula:

Elagolix sodium is a white to off white to light yellow powder and is freely soluble in water.

ORILISSA 150 mg tablets are light pink, oblong, film-coated tablets with “EL 150” debossed on one side. Each tablet contains 155.2 mg of elagolix sodium (equivalent to 150 mg of elagolix) as the active ingredient and the following inactive ingredients: mannitol, sodium carbonate monohydrate, pregelatinized starch, povidone, magnesium stearate, polyvinyl alcohol, titanium dioxide, polyethylene glycol, talc, and carmine high tint.

ORILISSA 200 mg tablets are light orange, oblong, film-coated tablets with “EL 200” debossed on one side. Each tablet contains 207.0 mg of elagolix sodium (equivalent to 200 mg of elagolix) as the active ingredient and the following inactive ingredients: mannitol, sodium carbonate monohydrate, pregelatinized starch, povidone, magnesium stearate, polyvinyl alcohol, titanium dioxide, polyethylene glycol, talc, and iron oxide red.

12 CLINICAL PHARMACOLOGY

12.1 Mechanism of Action

ORILISSA is a GnRH receptor antagonist that inhibits endogenous GnRH signaling by binding competitively to GnRH receptors in the pituitary gland. Administration of ORILISSA results in dose-dependent suppression of luteinizing hormone (LH) and follicle-stimulating hormone (FSH), leading to decreased blood concentrations of the ovarian sex hormones, estradiol and progesterone.

12.2 Pharmacodynamics

Effect on Ovulation and Estradiol

In a 3-menstrual cycle study in healthy women, ORILISSA 150 mg once daily and 200 mg twice daily resulted in an ovulation rate of approximately 50% and 32%, respectively. In the Phase 3 trials in women with endometriosis, ORILISSA caused a dose-dependent reduction in median estradiol concentrations to approximately 42 pg/mL for 150 mg once daily regimen and 12 pg/mL for the 200 mg twice daily regimen.

Cardiac Electrophysiology

The effect of elagolix on the QTc interval was evaluated in a randomized, placebo- and positive-controlled, open-label, single-dose, crossover thorough QTc study in 48 healthy adult premenopausal women. Elagolix concentrations in subjects given a single dose of 1200 mg was 17-times higher than the concentration in subjects given elagolix 200 mg twice daily. There was no clinically relevant prolongation of the QTc interval.

12.3 Pharmacokinetics

The pharmacokinetic properties of ORILISSA in healthy subjects are summarized in Table 8. The steady state pharmacokinetic parameters under fasting conditions are summarized in Table 9.

Table 8. Pharmacokinetic Properties of ORILISSA in Healthy Subjects
Absorption
Tmax (h) | 1.0
Effect of high-fat meal (relative to fasting) | AUC: ↓24%, Cmax: ↓36%
Distribution
% Bound to human plasma proteins | 80
Blood-to-plasma ratio | 0.6
Metabolism
Metabolism | CYP3A (major) Minor pathways include: CYP2D6, CYP2C8, and uridine glucuronosyl transferases (UGTs)
Elimination
Major route of elimination | Hepatic metabolism
Terminal phase elimination half-life (t1/2) (h) | 4-6
% of dose excreted in urine | <3
% of dose excreted in feces | 90

Table 9. Mean (%CV) Steady State Pharmacokinetic Parameters of ORILISSA
Pharmacokinetic Parameter (Units) | 150 mg Once Daily N = 6 | 200 mg Twice Daily N = 7
Cmax (ng/mL) | 574 (29) | 774 (68)
AUCτ (ng●hr/mL) | 1292 (31) | 1725 (57)
CL/F (L/hr) | 123 (21) | 144 (43)
Vdss/F | 1674 (94) | 881 (38)
Rac | 0.98 (7) | 0.89 (19)
CV: Coefficient of variation
Cmax: peak concentration
AUCτ: area under the plasma concentration-time curve during the dosing interval (τ) i.e., 12 hours for twice daily regimen, 24 hours for once daily regimen.
CL/F: oral clearance
Vdss/F: apparent volume of distribution at steady state
Rac: drug accumulation ratio

Specific Populations

Patients with Renal Impairment

Elagolix exposures (Cmax and AUC) are not altered by renal impairment. The mean exposures are similar for women with moderate to severe or end stage renal disease (including women on dialysis) compared to women with normal renal function.

Patients with Hepatic Impairment

Elagolix exposures (Cmax and AUC) are similar between women with normal hepatic function and women with mild hepatic impairment. Elagolix exposures in women with moderate and severe hepatic impairment are approximately 3-fold and 7-fold, respectively, higher than exposures from women with normal hepatic function [see Use in Specific Populations (8.7)].

Racial or Ethnic Groups

No clinically meaningful difference in the pharmacokinetics of ORILISSA between White and Black subjects or between Hispanics and others was observed. There is no clinically meaningful difference in the pharmacokinetics of ORILISSA between Japanese and Han Chinese subjects.

Body weight/Body mass index

Body weight or body mass index does not affect the pharmacokinetics of ORILISSA.

Drug Interaction Studies

Drug interaction studies were performed with ORILISSA and other drugs that are likely to be co-administered and with drugs commonly used as probes for pharmacokinetic interactions. Tables 10 and 11 summarize the pharmacokinetic effects when elagolix was co-administered with these drugs.

Table 10. Drug Interactions: Change in Pharmacokinetics of Elagolix in the Presence of Co-administered Drugs
Co- administered Drug | Regimen of Co- administered Drug | Regimen of Elagolix | N | Ratio (90% CI)*
Ketoconazole | 400 mg once daily | 150 mg single dose | 11 | Cmax | AUC
 |  |  |  | 1.77 (1.48 – 2.12) | 2.20 (1.98 – 2.44)
Rifampin# | 600 mg single dose | 150 mg single dose | 12 | 4.37 (3.62 – 5.28) | 5.58 (4.88 – 6.37)
 | 600 mg once daily |  |  | 2.00 (1.66 – 2.41) | 1.65 (1.45 – 1.89)
CI: Confidence interval
*ratios for Cmax and AUC compare co-administration of the medication with elagolix vs. administration of elagolix alone.
# A single dose of 600 mg rifampin inhibits OATP1B1; 600 mg once daily dose of rifampin inhibits OATP1B1 and induces CYP3A.

No clinically significant changes in elagolix exposures were observed when co-administered with rosuvastatin (20 mg once daily), sertraline (25 mg once daily) or fluconazole (200 mg single dose).

Table 11. Drug Interactions: Change in Pharmacokinetics of Co-administered Drug in the Presence of Elagolix
Co- administered Drug | Regimen of Co- administered Drug | Regimen of Elagolix | N | Ratio (90% CI)*
Digoxin | 0.5 mg single dose | 200 mg twice daily x 10 days | 11 | Cmax | AUC
 |  |  |  | 1.71 (1.53 – 1.91) | 1.26 (1.17 – 1.35)
Rosuvastatin | 20 mg once daily | 300 mg twice daily x 7 days | 10 | 0.99 (0.73 – 1.35) | 0.60 (0.50 – 0.71)
Midazolam | 2 mg single dose | 300 mg twice daily x 11 days | 20 | 0.56 (0.51 – 0.62) | 0.46 (0.41 – 0.50)
 |  | 150 mg once daily x 13 days | 11 | 0.81 (0.74 – 0.89) | 0.65 (0.58 – 0.72)
Norethindrone | 0.35 mg once daily x 112 days | 150 mg once daily x 56 days | 32 | 0.95 (0.86 – 1.05) | 0.88 (0.79 – 0.99)
Ethinyl Estradiol | Ethinyl estradiol 35 mcg and triphasic norgestimate 0.18/0.215/0.25 mg once daily | 150 mg once daily | 21 | 1.15 (1.07 – 1.25) | 1.30 (1.19 – 1.42)
Norelgestromina |  |  |  | 0.87 (0.78 – 0.97) | 0.85 (0.78 – 0.92)
Norgestrela |  |  |  | 0.89 (0.78 – 1.00) | 0.92 (0.84 – 1.01)
Ethinyl Estradiol | Ethinyl estradiol 20 mcg/Levonorgestrel 0.1 mg single dose | 200 mg twice daily x 15 days | 20 | 1.36 (1.27 – 1.45) | 2.18 (1.99 – 2.39)
Levonorgestrel |  |  |  | 0.97 (0.88 – 1.07) | 0.73 (0.64 – 0.82)
Omeprazole | 40 mg single dose | 300 mg twice daily x 9 days | 20 | 1.95 (1.50 – 2.53) | 1.78 (1.39 – 2.27)
CI: Confidence interval
*ratios for Cmax and AUC compare co-administration of the medication with elagolix vs. administration of the medication alone.
a metabolite of norgestimate

No clinically significant changes were observed in exposures of sertraline, fluconazole, or bupropion when co-administered with elagolix 300 mg twice daily.

12.5 Pharmacogenomics

Hepatic uptake of elagolix involves the OATP 1B1 transporter protein. Higher plasma concentrations of elagolix have been observed in patients who have two reduced function alleles of the gene that encodes OATP 1B1 (SLCO1B1 521T>C) (these patients are likely to have reduced hepatic uptake of elagolix and thus, higher plasma elagolix concentrations). The frequency of this SLCO1B1 521 C/C genotype is generally less than 5% in most racial/ethnic groups. Subjects with this genotype are expected to have a 78% mean increase in elagolix concentrations compared to subjects with normal transporter function (i.e., SLCO1B1 521T/T genotype). Adverse effects of elagolix have not been fully evaluated in subjects who have two reduced function alleles of the gene that encodes OATP1B1 (SLCO1B1 521T>C).

13 NONCLINICAL TOXICOLOGY

13.1 Carcinogenesis, Mutagenesis, Impairment of Fertility

Two-year carcinogenicity studies conducted in mice (50, 150, or 500 mg/kg/day) and rats (150, 300, or 800 mg/kg/day) that administered elagolix by the dietary route revealed no increase in tumors in mice at up to 19-fold the MRHD based on AUC. In the rat, there was an increase in thyroid (male and female) and liver (males only) tumors at the high dose (12 to 13-fold the MRHD). The rat tumors were likely species-specific and of negligible relevance to humans.

Elagolix was not genotoxic or mutagenic in a battery of tests, including the in vitro bacterial reverse mutation assay, the in vitro mammalian cell forward mutation assay at the thymidine kinase (TK+/-) locus in L5178Y mouse lymphoma cells, and the in vivo mouse micronucleus assay.

In a fertility study conducted in the rat, there was no effect of elagolix on fertility at any dose (50, 150, or 300 mg/kg/day). Based on AUC, the exposure multiple for the MRHD in women compared to the highest dose of 300 mg/kg/day in female rats is approximately 5-fold. However, because elagolix has low affinity for the GnRH receptor in the rat [see Use in Specific Populations (8.1)], and because effects on fertility are most likely to be mediated via the GnRH receptor, these data have low relevance to humans.

14 CLINICAL STUDIES

The efficacy of ORILISSA 150 mg once daily and 200 mg twice daily for the management of moderate to severe pain associated with endometriosis was demonstrated in two multinational double-blind, placebo-controlled trials in 1686 premenopausal women [Study EM-1 (NCT01620528) and Study EM-2 (NCT01931670)]. The median age of women in the trials was 32 years; 88% were White, 9% were Black or African American and 3% were other races. Each placebo-controlled trial assessed the reduction in endometriosis-associated pain over 6 months of treatment.

Moderate to severe pain associated with endometriosis was required for entry into the trials and was assessed during screening using the composite pelvic signs and symptoms score (CPSSS) and other baseline criteria.

The CPSSS is based on a modified Biberoglu and Behrman scale with five elements: three responses reported by study subjects (dysmenorrhea, dyspareunia, and non-menstrual pelvic pain) and two findings based on investigator assessment during physical examination (rating of pelvic tenderness and induration). Each element is scored from 0 (absent) to 3 (severe) for a maximum total score of 15. A total score of at least 6, with a score of at least 2 for dysmenorrhea and at least 2 for non-menstrual pelvic pain was required to qualify for randomization. Subjects were also required to have non-menstrual pelvic pain for at least four days in the preceding calendar month, defined as 35 days. Other criteria to determine eligibility for randomization included subject responses in a daily electronic diary (Endometriosis Daily Pain Impact Scale, described below) for both dysmenorrhea and non-menstrual pelvic pain in the 35 days prior to randomization.

Dysmenorrhea and Non-Menstrual Pelvic Pain

The co-primary efficacy endpoints were (1) the proportion of subjects whose dysmenorrhea responded to treatment at Month 3 and (2) the proportion of subjects whose pelvic pain not related to menses (also known as non-menstrual pelvic pain) responded to treatment at Month 3. Dysmenorrhea and non-menstrual pelvic pain were evaluated daily using the Endometriosis Daily Pain Impact Scale that asked subjects to rate their pain severity and its impact on daily activities during the prior 24 hours as none, mild, moderate or severe (correlating with a score of 0 to 3, respectively, where higher scores indicated greater severity). Scores at baseline and at each month were averaged over a 35-day interval.

Women were defined as responders if they experienced a reduction in dysmenorrhea and non-menstrual pelvic pain as defined in Table 12 with no increase in analgesic use (nonsteroidal anti-inflammatory drug or opioid) for endometriosis-associated pain. The threshold for defining responders was based on a receiver operating characteristic (ROC) analysis using the patient global impression of change as an anchor. A higher proportion of women treated with ORILISSA 150 mg once daily or 200 mg twice daily were responders for dysmenorrhea and non-menstrual pelvic pain compared to placebo in a dose-dependent manner at Month 3 [see Table 12].

Table 12. Proportion of Responders† for Dysmenorrhea and Non-Menstrual Pelvic Pain at Month 3 in Studies EM-1 and EM-2, Using the Endometriosis Daily Pain Impact Scale
 | Study EM-1 |  |  | Study EM-2
 | ORILISSA |  | Placebo | ORILISSA |  | Placebo
 | 150 mg Once Daily N=248 | 200 mg Twice Daily N=244 | N=373 | 150 mg Once Daily N=221 | 200 mg Twice Daily N=225 | N=353
Dysmenorrhea Difference from placebo | 46% 27%** | 76% 56%** | 20% | 43% 21%** | 72% 50%** | 23%
Non-Menstrual Pelvic Pain Difference from placebo | 50% 14%** | 55% 18%** | 36% | 50% 13%* | 58% 21%** | 37%
† Study EM-1-Dysmenorrhea responder threshold: at least 0.81 point decrease from baseline in dysmenorrhea score; Non-Menstrual Pelvic Pain responder threshold: at least 0.36 point decrease from baseline in Non-Menstrual Pelvic Pain score
Study EM-2 - Dysmenorrhea responder threshold: at least 0.85 point decrease from baseline in dysmenorrhea score; Non-Menstrual Pelvic Pain responder threshold: at least 0.43 point decrease from baseline in Non-Menstrual Pelvic Pain score
*p ≤0.01 for test of difference from placebo
**p≤0.001 for test of difference from placebo

Women in these studies also provided a daily self-assessment of their endometriosis pain using a numeric rating scale (NRS) that asked subjects to rate their endometriosis pain at its worst over the last 24 hours on a scale from 0 (no pain) to 10 (worst pain ever). In Study EM-1, baseline NRS scores were 5.7 for ORILISSA 150 mg once daily, 5.5 for ORILISSA 200 mg twice daily and 5.6 for placebo. In Study EM-2, baseline NRS scores were 5.7 for ORILISSA 150 mg once daily, 5.3 for ORILISSA 200 mg twice daily and 5.6 for placebo. Women taking ORILISSA 150 mg once daily and 200 mg twice daily reported a statistically (p <0.001) significant reduction from baseline in NRS scores compared to placebo at Month 3 in both Studies EM-1 and EM-2 (Study EM-1: 0.7 points for ORILISSA 150 mg once daily and 1.3 points for ORILISSA 200 mg twice daily; Study EM-2: 0.6 points for ORILISSA 150 mg once daily and 1.2 points for ORILISSA 200 mg twice daily).

In addition, both ORILISSA treatment groups showed statistically significantly greater mean decreases from baseline compared to placebo in dysmenorrhea and non-menstrual pelvic pain scores at Month 6. Figures 3 through 6 show the mean scores for dysmenorrhea and non-menstrual pelvic pain over time for Study EM-1 and EM-2.

Figure 3. Mean Dysmenorrhea Pain Scoresa in Study EM-1 Over 6 Months | Figure 4. Mean Dysmenorrhea Pain Scoresa in Study EM-2 Over 6 Months

Figure 5. Mean Non-Menstrual Pelvic Paina Scores in Study EM-1 Over 6 Months | Figure 6. Mean Non-Menstrual Pelvic Paina Scores in Study EM-2 Over 6 Months

Dyspareunia

Dyspareunia associated with endometriosis was evaluated as a secondary endpoint using the Endometriosis Daily Pain Impact Scale that asked subjects to rate their pain during sexual intercourse in the prior 24 hours as none, mild, moderate, severe (correlating with a score of 0 to 3, respectively, where higher scores indicated greater severity), or not applicable. In both Studies EM-1 and EM-2, women treated with ORILISSA 200 mg twice daily showed statistically significantly greater reduction in dyspareunia from baseline to Month 3 than women given placebo (Study EM-1: 0.2; Study EM-2: 0.3). Figures 7 and 8 show the mean scores over time for Study EM-1 and EM-2.

Figure 7. Mean Dyspareunia Scoresa in Study EM-1 Over 3 Months | Figure 8. Mean Dyspareunia Scoresa in Study EM-2 Over 3 Months

Use of rescue pain medication

In EM-1 and EM-2, 59% and 60% of patients used an opioid rescue analgesic for pain at baseline. The opioid rescue analgesics used at baseline were predominantly hydrocodone/acetaminophen (HC/APAP) and codeine/APAP at strengths of 5/300-325 mg and 30/300-500 mg. In EM-1, of all patients on an opioid at baseline, 98% and 2% were on HC/APAP and codeine/APAP, respectively. In EM-2, of all patients on an opioid at baseline, 50% were on HC/APAP and 16% were on codeine/APAP.

Other data related to opioid rescue analgesic use are summarized in Table 13.

Table 13. Opioid Rescue Analgesic Use in EM-1 and EM-2
 | Study EM-1 |  |  | Study EM-2
 | ORILISSA 150 mg Once Daily | ORILISSA 200 mg Twice Daily | Placebo | ORILISSA 150 mg Once Daily | ORILISSA 200 mg Twice Daily | Placebo
Tablets per month at baseline (mean±SD) | 15 ±24 | 15 ±25 | 13 ±21 | 13 ±29 | 12 ±26 | 12 ±21
Tablets per month at baseline [Median (Min, Max)] | 4 (0, 184) | 4 (0, 195) | 4 (0, 146) | 4 (0, 236) | 3 (0, 214) | 4 (0, 152)
Tablets per month at Month 3 (mean±SD) | 12 ±29 | 7 ±18 | 10 ±17 | 8 ±22 | 5 ±14 | 8 ±15
Tablets per month at Month 3 [Median (Min, Max)] | 0 (0, 251) | 0 (0, 162) | 2 (0, 144) | 0 (0, 168) | 0 (0, 136) | 2 (0, 142)
Tablets per month at Month 6 (mean±SD) | 11 ±26 | 7 ±17 | 11 ±19 | 7 ±19 | 5 ±14 | 8 ±15
Tablets per month at Month 6 [Median (Min, Max)] | 0 (0, 224) | 0 (0, 157) | 3 (0, 185) | 0 (0, 185) | 0 (0, 157) | 2 (0, 142)
Number and % of patients on any dose of opioid rescue at baseline who were off opioid at Month 3* | 46/150 (31%) | 59/151 (39%) | 36/211 (17%) | 44/124 (35%) | 68/134 (51%) | 54/220 (25%)
Number and % of patients on any dose of opioid rescue at baseline who were off opioid at Month 6* | 43/149 (29%) | 66/150 (44%) | 36/211 (17%) | 50/124 (40%) | 78/134 (58%) | 70/222 (32%)
Number and % of patients not on opioid rescue at baseline who were on any opioid at Month 3^ | 9/98 (9%) | 6/93 (6%) | 17/162 (10%) | 10/97 (10%) | 10/91 (11%) | 29/133 (22%)
Number and % of patients not on opioid rescue at baseline who were on any opioid at Month 6^ | 16/98 (16%) | 6/93 (6%) | 32/161 (20%) | 13/97 (13%) | 6/91 (7%) | 32/133 (24%)
Min = minimum; Max = maximum; SD = standard deviation
Monthly calculations are based on a 35-day interval.
*Denominator is the number of subjects on opioid rescue at baseline.
^Denominator is the number of subjects not on opioid rescue at baseline.

The clinical relevance of these data has not been demonstrated.

16 HOW SUPPLIED/STORAGE AND HANDLING

ORILISSA tablets are available in two strengths: 150 mg and 200 mg, which are equivalent to 155.2 mg and 207.0 mg of elagolix sodium, respectively.

ORILISSA 150 mg tablets are light pink, oblong, film-coated tablets with “EL 150” debossed on one side. ORILISSA 150 mg tablets are packaged in weekly blister packs. Each blister pack contains 7 tablets supplying the drug product for one week. Four blister packs (a total of 28 tablets) are packaged into a carton that provides the drug product for 4 weeks (NDC 0074-0038-28).

ORILISSA 200 mg tablets are light orange, oblong, film-coated tablets with “EL 200” debossed on one side. The 200 mg tablets are packaged in weekly blister packs. Each blister pack contains 14 tablets supplying the drug product for one week. Four blister packs (a total of 56 tablets) are packaged in a carton that provides the drug product for 4 weeks (NDC 0074-0039-56).

Store at 2°C to 30°C (36°F to 86°F).

Dispose unused medication via a take-back option if available. Otherwise, follow FDA instructions for disposing medication in the household trash, www.fda.gov/drugdisposal. Do NOT flush down the toilet.

17 PATIENT COUNSELING INFORMATION

Advise patients to read the FDA-approved patient labeling (Medication Guide).

Bone Loss

Inform patients about the risk of bone loss. Advise patients that supplementary calcium and vitamin D may be beneficial if dietary intake of calcium and vitamin D is not adequate [see Warnings and Precautions (5.1)].

Change in Menstrual Bleeding Pattern, Contraception and Pregnancy

Advise women that ORILISSA may delay the recognition of pregnancy because it may reduce the amount, intensity, or duration of menstrual bleeding. Advise patients to use effective non-hormonal contraception while taking ORILISSA and to discontinue ORILISSA if pregnancy is confirmed [see Warnings and Precautions (5.2) and Use in Specific Populations (8.1)].

Suicidal Ideation, Suicidal Behavior, and Exacerbation of Mood Disorders

Advise patients that suicidal ideation and exacerbation of mood disorders may occur with ORILISSA use. Instruct patients to seek immediate medical attention for suicidal ideation and behavior and for new onset or worsening depression, anxiety, or other mood changes [see Warnings and Precautions (5.3)].

Liver Injury

Advise patients to promptly seek medical attention in case of signs or symptoms that may reflect liver injury, such as jaundice [see Warnings and Precautions (5.4)].

ORILISSA Missed Dose Instructions

Instruct a patient who miss a dose of ORILISSA to take the missed dose on the same day as soon as she remembers and then resume the regular dosing schedule:

- 150 mg once daily: no more than 1 tablet each day should be taken.
- 200 mg twice daily: no more than 2 tablets each day should be taken.

ORILISSA Disposal Instructions

Instruct patients to dispose of unused medication via a take-back option if available or to otherwise follow FDA instructions for disposing of medication in the household trash, www.fda.gov/drugdisposal, and NOT to flush down the toilet.

Manufactured by AbbVie Inc. North Chicago, IL 60064

ORILISSA is a trademark of AbbVie Inc.

© 2025 AbbVie Inc. All rights reserved.

20096645 December 2025

MEDICATION GUIDE
ORILISSA® (awr-ah-lih-sah)
(elagolix)
tablets, for oral use

What is the most important information I should know about ORILISSA?
ORILISSA may cause serious side effects, including:

- bone loss (decreased bone mineral density).
  ○ While you are taking ORILISSA, your estrogen levels will be low. Low estrogen levels can lead to bone mineral density loss.
  ○ If you have bone loss on ORILISSA, your bone density may improve after you stop taking ORILISSA but complete recovery may not occur. It is unknown if these bone changes could increase your risk for broken bones as you age. For this reason, your healthcare provider may limit the length of time you take ORILISSA.
  ○ Your healthcare provider may advise you to take vitamin D and calcium supplements as part of a healthy lifestyle that promotes bone health.
  ○ If you have conditions or take other medicines that can cause bone loss, or if you have broken a bone with minimal or no injury, your healthcare provider may order an X-ray test called a DXA scan to check your bone mineral density.
- effects on pregnancy
  ○ Do not take ORILISSA if you are trying to become or are pregnant. It may increase the risk of early pregnancy loss.
  ○ If you think you are pregnant, stop taking ORILISSA right away and call your healthcare provider.
  ○ ORILISSA may change your menstrual periods (irregular bleeding or spotting, a decrease in menstrual bleeding, or no bleeding at all), making it hard to know if you are pregnant. Watch for other signs of pregnancy such as breast tenderness, weight gain and nausea.
  ○ ORILISSA does not prevent pregnancy. You will need to use effective methods of birth control while taking ORILISSA and for 28 days after you stop taking ORILISSA. Examples of effective methods can include condoms or spermicide, which do not contain hormones.
  ○ Birth control pills that contain estrogen may make ORILISSA less effective. It is not known how well ORILISSA will work while you are taking progestin-only birth control such as injections or implants.
  ○ Talk to your healthcare provider about which birth control to use during treatment with ORILISSA. Your healthcare provider may change the birth control you were on before you start taking ORILISSA.

What is ORILISSA?
ORILISSA is a prescription medicine used to treat moderate to severe pain associated with endometriosis. It is not known if ORILISSA is safe and effective in children.

Do not take ORILISSA if you:

- are pregnant
- have osteoporosis
- have severe liver disease
- are taking medicines called organic anion transporting polypeptide (OATP)1B1 inhibitors that are known or expected to significantly increase the blood levels of elagolix (the active ingredient in ORILISSA). Ask your healthcare provider if you are not sure if you are taking one of these medicines.
- have had a serious allergic reaction to ORILISSA or any of the ingredients in ORILISSA. See the end of this Medication Guide for a complete list of ingredients in ORILISSA. Ask your healthcare provider if you are not sure.

Before you take ORILISSA, tell your healthcare provider about all of your medical conditions, including if you:

- have or have had broken bones or other conditions that may cause bone problems
- have or have had depression, mood problems or suicidal thoughts or behavior
- have liver problems
- think you may be pregnant. You should avoid becoming pregnant while taking ORILISSA
- are breastfeeding or plan to breastfeed. It is not known if ORILISSA passes into your breastmilk. Talk to your healthcare provider about the best way to feed your baby if you take ORILISSA.

Tell your healthcare provider about all the medicines you take, including prescription and over-the-counter medicines, vitamins, and herbal supplements.
Especially tell your healthcare provider if you take:

- birth control that contains hormones. Your healthcare provider may advise you to change your method of birth control.

Know the medicines you take. Keep a list of your medicines with you to show to your healthcare provider and pharmacist when you get a new medicine.

How should I take ORILISSA?

- Take ORILISSA exactly as your healthcare provider tells you to take it.
- Your healthcare provider will give you a pregnancy test before you start taking ORILISSA or will have you start taking ORILISSA within 7 days after you start your period.
- If your healthcare provider prescribes:
  ○ ORILISSA 150 mg (a pink tablet), take it 1 time each day
  ○ ORILISSA 200 mg (an orange tablet), take it 2 times each day
- Take ORILISSA at about the same time each day with or without food.
- If you take too much ORILISSA, call your healthcare provider or go to the nearest hospital emergency room right away.
- If you miss a dose of ORILISSA:
  ○ 150 mg (1 time each day), take it as soon as you remember as long as it is on the same day. Do not take more than 1 tablet each day.
  ○ 200 mg (2 times each day), take it as soon as you remember as long as it is on the same day. Do not take more than 2 tablets each day.

What are the possible side effects of ORILISSA?
ORILISSA may cause serious side effects including:

- See “What is the most important information I should know about ORILISSA?”
- suicidal thoughts, suicidal behavior, and worsening of mood. ORILISSA may cause suicidal thoughts or actions. Call your healthcare provider or get emergency medical help right away if you have any of the following symptoms, especially if they are new, worse, or bother you:
  ○ thoughts about suicide or dying
  ○ attempts to commit suicide
  ○ new or worse depression
  ○ new or worse anxiety
  ○ other unusual changes in behavior or mood

You or your caregiver should pay attention to any changes, especially sudden changes in your mood, behaviors, thoughts, or feelings.

- abnormal liver tests. Call your healthcare provider right away if you have any of these signs and symptoms of liver problems:
  ○ yellowing of the skin or the whites of the eyes (jaundice)
  ○ dark amber-colored urine
  ○ feeling tired (fatigue or exhaustion)
  ○ nausea and vomiting
  ○ generalized swelling
  ○ right upper stomach area (abdomen) pain
  ○ bruising easily

The most common side effects of ORILISSA include: hot flashes and night sweats, headache, nausea, difficulty sleeping, absence of periods, anxiety, joint pain, depression and mood changes.
These are not all the possible side effects of ORILISSA. Call your healthcare provider for medical advice about side effects.
You may report side effects to FDA at 1-800-FDA-1088.

How should I store ORILISSA?

- Store ORILISSA between 36°F to 86°F (2°C to 30°C).
- Do not keep medicine that is out of date or that you no longer need.
- Throw away (dispose of) unused medicines through community take-back disposal programs when available. If no community take-back disposal program is available go to www.fda.gov/drugdisposal for more information on how to dispose of ORILISSA the right way.
- Do not flush ORILISSA down the toilet.
- Keep ORILISSA and all medicines out of the reach of children.

General information about the safe and effective use of ORILISSA.
Medicines are sometimes prescribed for purposes other than those listed in a Medication Guide. Do not use ORILISSA for a condition for which it was not prescribed. Do not give ORILISSA to other people, even if they have the same symptoms that you have. It may harm them. You can ask your pharmacist or healthcare provider for information about ORILISSA that is written for health professionals.

What are the ingredients in ORILISSA?
Active ingredient: elagolix
Inactive ingredients 150 mg tablets: mannitol, sodium carbonate monohydrate, pregelatinized starch, povidone, magnesium stearate, polyvinyl alcohol, titanium dioxide, polyethylene glycol, talc, and carmine high tint.
Inactive ingredients 200 mg tablets: mannitol, sodium carbonate monohydrate, pregelatinized starch, povidone, magnesium stearate, polyvinyl alcohol, titanium dioxide, polyethylene glycol, talc, and iron oxide red.
Manufactured by
AbbVie Inc.
North Chicago, IL 60064
20096645
For more information, go to www.orilissa.com or call 1-844-674-3676.

This Medication Guide has been approved by the U.S. Food and Drug Administration Revised: December 2025

PACKAGE LABEL

NDC 0074-0038-01

Rx only

7 TABLETS

FOR 7 DAYS

Orilissa®

elagolix tablets 150 mg

150 mg per tablet

Orilissa (elagolix) Tablets,

150 mg equivalent to 155.2 mg elagolix sodium

PACKAGE LABEL

NDC 0074-0038-28

Rx only

28 TABLETS

FOR 28 DAYS

Orilissa®

elagolix tablets 150 mg

150 mg per tablet

Orilissa (elagolix) Tablets,

150 mg equivalent to 155.2 mg elagolix sodium

Each carton contains 28 tablets in 4 weekly blister packs

Each weekly blister pack contains 7 tablets of elagolix 150 mg

PACKAGE LABEL

NDC 0074-0039–01

Rx only

14 TABLETS

FOR 7 DAYS

Orilissa®

elagolix tablets 200 mg

200 mg per tablet

Orilissa (elagolix) Tablets,

200 mg equivalent to 207.0 mg elagolix sodium

PACKAGE LABEL

NDC 0074-0039-56

Rx only

56 TABLETS

FOR 28 DAYS

Orilissa®

elagolix tablets 200 mg

200 mg per tablet

Orilissa (elagolix) Tablets,

200 mg equivalent to 207.0 mg elagolix sodium

Each carton contains 56 tablets in 4 weekly blister packs

Each weekly blister pack contains 14 tablets of elagolix 200 mg